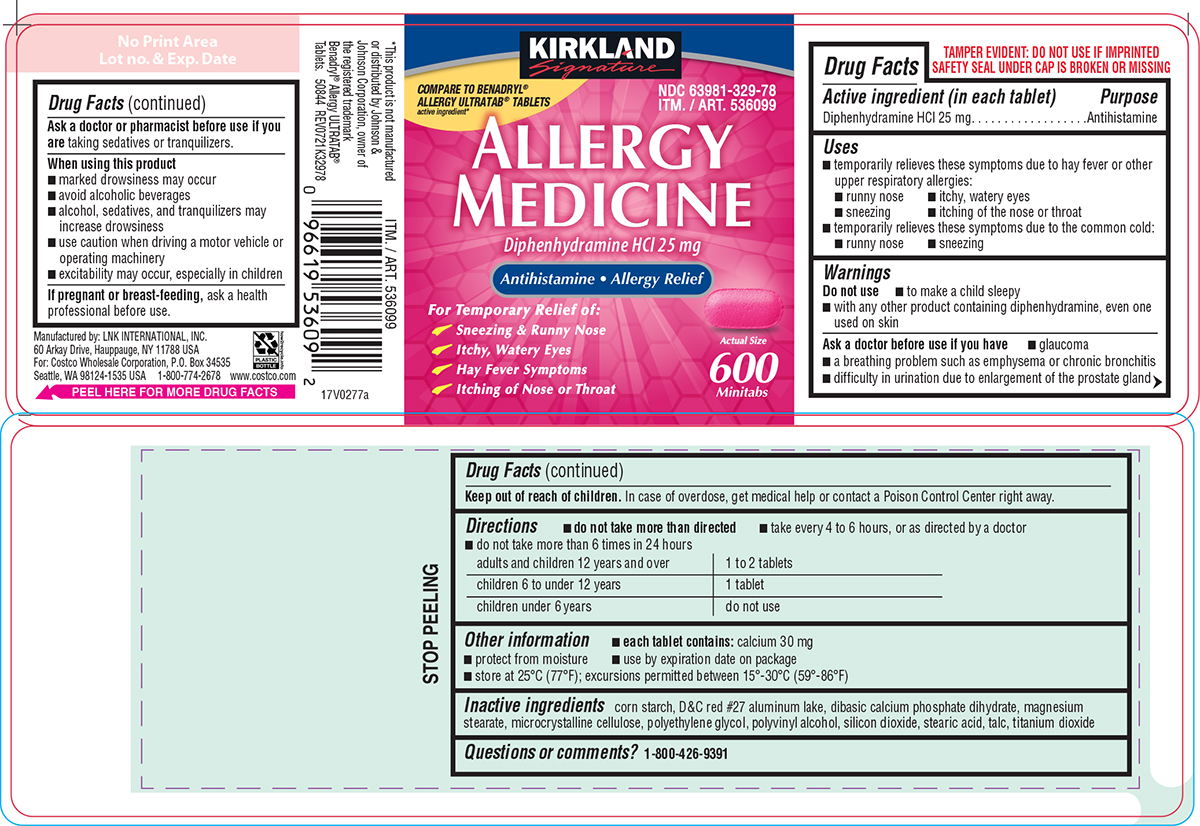 DRUG LABEL: Allergy Medicine
NDC: 63981-329 | Form: TABLET, FILM COATED
Manufacturer: COSTCO WHOLESALE CORPORATION
Category: otc | Type: HUMAN OTC DRUG LABEL
Date: 20250414

ACTIVE INGREDIENTS: DIPHENHYDRAMINE HYDROCHLORIDE 25 mg/1 1
INACTIVE INGREDIENTS: STARCH, CORN; D&C RED NO. 27 ALUMINUM LAKE; DIBASIC CALCIUM PHOSPHATE DIHYDRATE; MAGNESIUM STEARATE; MICROCRYSTALLINE CELLULOSE; POLYETHYLENE GLYCOL, UNSPECIFIED; POLYVINYL ALCOHOL, UNSPECIFIED; SILICON DIOXIDE; STEARIC ACID; TALC; TITANIUM DIOXIDE

Kirkland 44-329

Active ingredient (in each tablet)

Diphenhydramine HCl 25 mg

Purpose

Antihistamine

Uses

- temporarily relieves these symptoms due to hay fever or other upper respiratory allergies:
  - runny nose
  - itchy, watery eyes
  - sneezing
  - itching of the nose or throat
- temporarily relieves these symptoms due to the common cold:
  - runny nose
  - sneezing

Warnings

Do not use

- to make a child sleepy
- with any other product containing diphenhydramine, even one used on skin

Ask a doctor before use if you have

- glaucoma
- a breathing problem such as emphysema or chronic bronchitis
- difficulty in urination due to enlargement of the prostate gland

Ask a doctor or pharmacist before use if you are

taking sedatives or tranquilizers.

When using this product

- marked drowsiness may occur
- avoid alcoholic beverages
- alcohol, sedatives, and tranquilizers may increase drowsiness
- use caution when driving a motor vehicle or operating machinery
- excitability may occur, especially in children

If pregnant or breast-feeding,

ask a health professional before use.

Keep out of reach of children.

In case of overdose, get medical help or contact a Poison Control Center right away.

Directions

- do not take more than directed
- take every 4 to 6 hours, or as directed by a doctor
- do not take more than 6 times in 24 hours

adults and children 12 years and over | 1 to 2 tablets
children 6 to under 12 years | 1 tablet
children under 6 years | do not use

Other information

- each tablet contains: calcium 30 mg
- protect from moisture
- use by expiration date on package
- store at 25°C (77°F); excursions permitted between 15°-30°C (59°-86°F)

Inactive ingredients

corn starch, D&C red #27 aluminum lake, dibasic calcium phosphate dihydrate, magnesium stearate, microcrystalline cellulose, polyethylene glycol, polyvinyl alcohol, silicon dioxide, stearic acid, talc, titanium dioxide

Questions or comments?

1-800-426-9391

Principal Display Panel

KIRKLAND
Signature

COMPARE TO BENADRYL®
ALLERGY ULTRATAB® TABLETS
active ingredient*

NDC 63981-329-78
ITM. / ART. 536099

ALLERGY
MEDICINE

Diphenhydramine HCl 25 mg

Antihistamine • Allergy Relief

For Temporary Relief of:
Sneezing & Runny Nose
Itchy, Watery Eyes
Hay Fever Symptoms
Itching of Nose or Throat

Actual Size

600
Minitabs

TAMPER EVIDENT: DO NOT USE IF IMPRINTED
SAFETY SEAL UNDER CAP IS BROKEN OR MISSING

*This product is not manufactured
or distributed by Johnson &
Johnson Corporation, owner of
the registered trademark
Benadryl® Allergy ULTRATAB®
Tablets. 50844 REV0721K32978

Manufactured by: LNK INTERNATIONAL, INC.
60 Arkay Drive, Hauppauge, NY 11788 USA
For: Costco Wholesale Corporation, P.O. Box 34535
Seattle, WA 98124-1535 USA 1-800-774-2678 www.costco.com

Kirkland 44-329